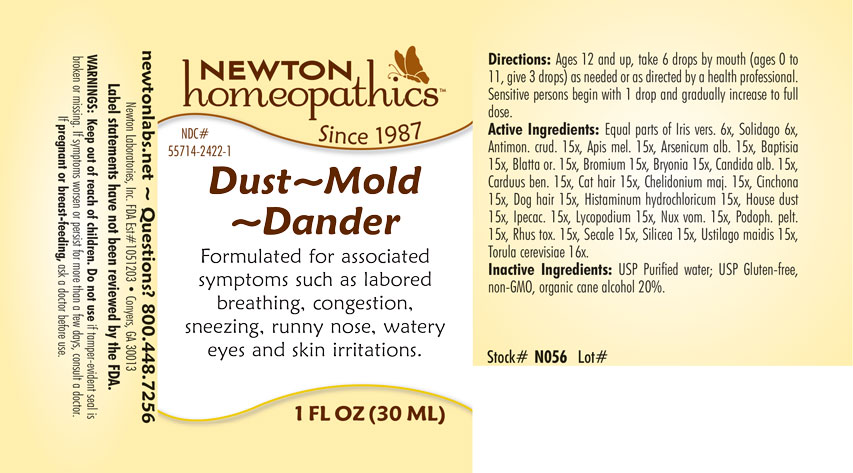 DRUG LABEL: Dust-Mold-Dander
NDC: 55714-2422 | Form: LIQUID
Manufacturer: Newton Laboratories, Inc.
Category: homeopathic | Type: HUMAN OTC DRUG LABEL
Date: 20250206

ACTIVE INGREDIENTS: HOUSE DUST 15 [hp_X]/1 mL; IRIS VERSICOLOR ROOT 6 [hp_X]/1 mL; ANTIMONY TRISULFIDE 15 [hp_X]/1 mL; APIS MELLIFERA 15 [hp_X]/1 mL; ARSENIC TRIOXIDE 15 [hp_X]/1 mL; BAPTISIA TINCTORIA ROOT 15 [hp_X]/1 mL; BLATTA ORIENTALIS 15 [hp_X]/1 mL; BROMINE 15 [hp_X]/1 mL; BRYONIA ALBA ROOT 15 [hp_X]/1 mL; CANDIDA ALBICANS 15 [hp_X]/1 mL; CENTAUREA BENEDICTA 15 [hp_X]/1 mL; FELIS CATUS HAIR 15 [hp_X]/1 mL; CHELIDONIUM MAJUS 15 [hp_X]/1 mL; CINCHONA OFFICINALIS BARK 15 [hp_X]/1 mL; CANIS LUPUS FAMILIARIS HAIR 15 [hp_X]/1 mL; HISTAMINE DIHYDROCHLORIDE 15 [hp_X]/1 mL; IPECAC 15 [hp_X]/1 mL; LYCOPODIUM CLAVATUM SPORE 15 [hp_X]/1 mL; STRYCHNOS NUX-VOMICA SEED 15 [hp_X]/1 mL; PODOPHYLLUM 15 [hp_X]/1 mL; TOXICODENDRON PUBESCENS LEAF 15 [hp_X]/1 mL; CLAVICEPS PURPUREA SCLEROTIUM 15 [hp_X]/1 mL; SILICON DIOXIDE 15 [hp_X]/1 mL; USTILAGO MAYDIS 15 [hp_X]/1 mL; SACCHAROMYCES CEREVISIAE 16 [hp_X]/1 mL; SOLIDAGO VIRGAUREA FLOWERING TOP 6 [hp_X]/1 mL
INACTIVE INGREDIENTS: WATER; ALCOHOL

Dust 2422L

INDICATIONS & USAGE SECTION

Formulated for associated symptoms such as labored breathing, congestion, sneezing, runny nose, watery eyes and skin irritations,

DOSAGE & ADMINISTRATION SECTION

Ages 12 and up, take 6 drops by mouth (ages 0 to 11, give 3 drops) as needed or as directed by a health professional. Sensitive persons begin with 1 drop and gradually increase to full dose.

OTC - ACTIVE INGREDIENT SECTION

Equal parts of Iris versicolor 6x, Solidago virgaurea 6x, Antimonium crudum 15x, Apis mellifica 15x, Arsenicum album 15x, Baptisia tinctoria 15x, Blatta orientalis 15x, Bromium 15x, Bryonia 15x, Candida albicans 15x, Carduus benedictus 15x, Cat hair 15x, Chelidonium majus 15x, Cinchona officinalis 15x, Dog hair 15x, Histaminum hydrochloricum 15x, House dust 15x, Ipecacuanha 15x, Lycopodium clavatum 15x, Nux vomica 15x, Podophyllum peltatum 15x, Rhus toxicodendron 15x, Secale cornutum 15x, Silicea 15x, Ustilago maidis 15x, Torula cerevisiae 16x.

OTC - PURPOSE SECTION

Formulated for associated symptoms such as labored breathing, congestion, sneezing, runny nose, watery eyes and skin irritations.

INACTIVE INGREDIENT SECTION

Inactive Ingredients: USP Purified Water; USP Gluten-free, non-GMO, organic cane alcohol 20%.

QUESTIONS SECTION

newtonlabs.net - Questions? 800.448.7256

Newton Laboratories, Inc. FDA Est # 1051203 Conyers, GA 30013

WARNINGS SECTION

WARNINGS: Keep out of reach of children. Do not use if tamper-evident seal is broken or missing. If symptoms worsen or persist for more than a few days, consult a doctor. If pregnant or breast-feeding, ask a doctor before use.

OTC - PREGNANCY OR BREAST FEEDING SECTION

If pregnant or breast-feeding, ask a doctor before use.

OTC - KEEP OUT OF REACH OF CHILDREN SECTION

Keep out of reach of children.